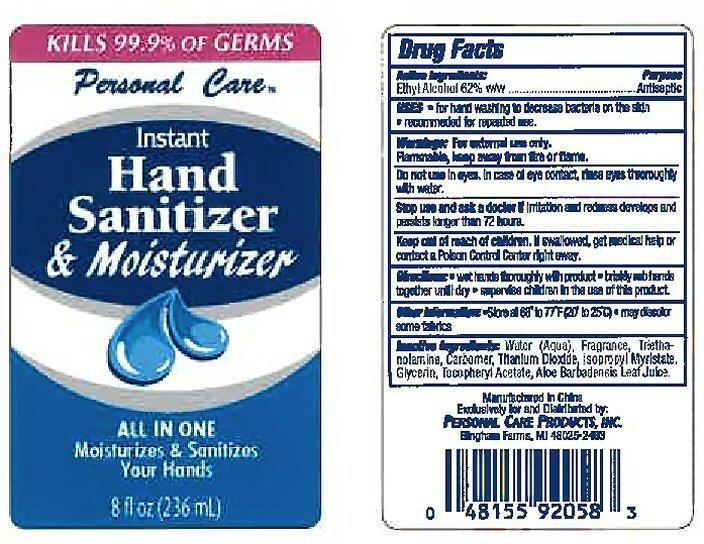 DRUG LABEL: Instant Hand Sanitizer and Moisterizer
                        
NDC: 29500-9086 | Form: LIQUID
Manufacturer: Personal Care Products
Category: otc | Type: HUMAN OTC DRUG LABEL
Date: 20130904

ACTIVE INGREDIENTS: ALCOHOL 146 mL/236 mL
INACTIVE INGREDIENTS: WATER; TROLAMINE; TITANIUM DIOXIDE; ISOPROPYL MYRISTATE; GLYCERIN; ALPHA-TOCOPHEROL ACETATE; ALOE VERA LEAF

Instant Hand Sanitizer and Moisterizer

Active Ingredients: Ethyl Alcohol 62% w/w

Purpose: Antiseptic

Keep out of reach of children. If swallowed, get medical help or contact a Poison Control Center right away.

Uses

- for hand washing to decrease bacteria on the skin
- recommended for repeated use.

Warnings: For external use only.

Flammable, keep away from fire or flame.

Do not use in eyes. In case of eye contact, rinse eyes thoroughly with water.

Stop use and ask a doctor if irritation and redness develops andd persists longer than 72 hours.

Directions:

Wet hands thoroughly with product

Briskly rub hands together until dry

Supervise children in the use of this product

INACTIVE INGREDIENT

Inactive ingredients: Water (Aqua), Fragrance, Triethanolamine, Carbomer, Titanium Dioxide, Isopropyl Myristate, Glycerin, Tocopheryl Acetate, Aloe Barbadensis Leaf Juice.

PACKAGE LABEL

Kills 99.9% of germs

Personal Care

Instant Hand Sanitizer and Moisterizer

All in one

Moisturizes and Sanitizes Your Hands

8 fl oz (236 ml)